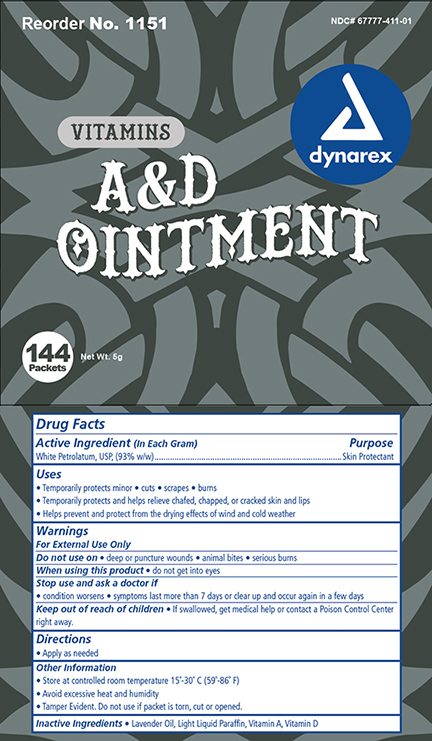 DRUG LABEL: Vitamin AD
NDC: 67777-411 | Form: OINTMENT
Manufacturer: Dynarex Corporation
Category: otc | Type: HUMAN OTC DRUG LABEL
Date: 20170405

ACTIVE INGREDIENTS: PETROLATUM .93 g/1 g
INACTIVE INGREDIENTS: VITAMIN A PALMITATE; LIGHT MINERAL OIL; CHOLECALCIFEROL; LAVENDER OIL

Vitamin A D

Active Ingredient Purpose

White Petrolatum USP (76%) Skin Protectant

Purpose:

- Temporarily protects minor * cuts * scrapes * burns
- Temporarily helps protect and help relieve chapped and cracked skin and lips
- Helps prevent and protect from the drying effects of wind and cold weather

Warnings:

For External Use Only

When using this product:

- Do not get in eyes

Stop use and ask a doctor if:

- If condition worsens
- symptoms last more than 7 days or clear up and occur again in a few days

Keep out of reach of children

- If swallowed, get medical help or contact a Poison Control Center right away.

Do not use on:

- Deep or puncture wounds
- animal bites
- serious burns

Dosage and Administration

- Apply as needed.

Directions

- Apply as needed

Other information:

- Store at room temperature 15 deg C to 30 deg C (59 deg F to 86 deg F)
- Avoid excessive heat and humidity
- Tamper Evident. Do not use if packet is torn, cut or opened.

Inactive Ingredients:

Inactive Ingredients: Lavender oil, Light Liquid Parafin, Vitamin A, Vitamin D

Principal Display Panel

1151 BX.jpg